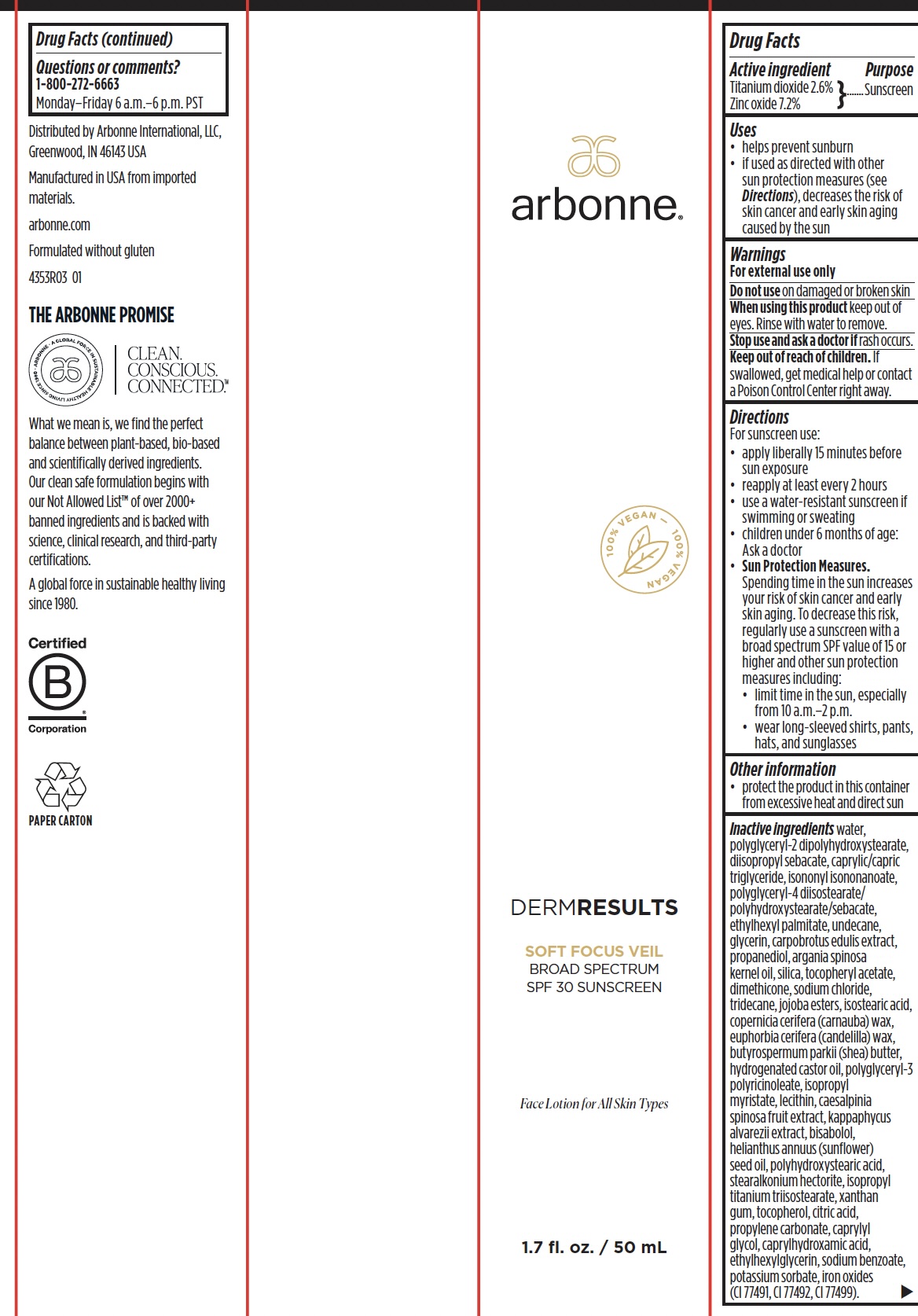 DRUG LABEL: Arbonne Soft Focus Veil Broad Spectrum SPF 30 Sunscreen
NDC: 42508-881 | Form: LOTION
Manufacturer: Arbonne International, LLC
Category: otc | Type: HUMAN OTC DRUG LABEL
Date: 20251209

ACTIVE INGREDIENTS: TITANIUM DIOXIDE 26 mg/1 mL; ZINC OXIDE 72 mg/1 mL
INACTIVE INGREDIENTS: WATER; DIISOPROPYL SEBACATE; MEDIUM-CHAIN TRIGLYCERIDES; ISONONYL ISONONANOATE; POLYGLYCERYL-4 DIISOSTEARATE/POLYHYDROXYSTEARATE/SEBACATE; ETHYLHEXYL PALMITATE; UNDECANE; GLYCERIN; PROPANEDIOL; ARGAN OIL; SILICON DIOXIDE; .ALPHA.-TOCOPHEROL ACETATE; DIMETHICONE; SODIUM CHLORIDE; TRIDECANE; HYDROGENATED JOJOBA OIL; ISOSTEARIC ACID; CARNAUBA WAX; CANDELILLA WAX; SHEA BUTTER; HYDROGENATED CASTOR OIL; POLYGLYCERYL-3 RICINOLEATE; ISOPROPYL MYRISTATE; LECITHIN, SUNFLOWER; LEVOMENOL; SUNFLOWER OIL; POLYHYDROXYSTEARIC ACID STEARATE; STEARALKONIUM HECTORITE; ISOPROPYL TITANIUM TRIISOSTEARATE; XANTHAN GUM; TOCOPHEROL; ANHYDROUS CITRIC ACID; PROPYLENE CARBONATE; CAPRYLYL GLYCOL; CAPRYLHYDROXAMIC ACID; ETHYLHEXYLGLYCERIN; SODIUM BENZOATE; POTASSIUM SORBATE; FERRIC OXIDE RED; FERRIC OXIDE YELLOW; FERROSOFERRIC OXIDE; POLYGLYCERYL-2 DIPOLYHYDROXYSTEARATE

Arbonne®Soft Focus Veil Broad Spectrum SPF 30 Sunscreen

Drug Facts

Active ingredient

Titanium dioxide 2.6%
Zinc oxide 7.2%

Purpose

Sunscreen

Uses

- helps prevent sunburn
- if used as directed with other sun protection measures (see Directions), decreases the risk of skin cancer and early skin aging caused by the sun

Warnings

For external use only

Do not useon damaged or broken skin

WHEN USING

When using this productkeep out of eyes. Rinse with water to remove.

Stop use and ask a doctor ifrash occurs.

Keep out of reach of children.If swallowed, get medical help or contact a Poison Control Center right away.

Directions

For sunscreen use:

- apply liberally 15 minutes before sun exposure
- reapply at least every 2 hours
- use a water-resistant sunscreen if swimming or sweating
- children under 6 months of age: Ask a doctor
- Sun Protection Measures.Spending time in the sun increases your risk of skin cancer and early skin aging. To decrease this risk, regularly use a sunscreen with a broad spectrum SPF value of 15 or higher and other sun protection measures including:
  - limit time in the sun, especially from 10 a.m.–2 p.m.
  - wear long-sleeved shirts, pants, hats, and sunglasses

Other information

- protect the product in this container from excessive heat and direct sun

Inactive ingredients

water, polyglyceryl-2 dipolyhydroxystearate, diisopropyl sebacate, caprylic/capric triglyceride, isononyl isononanoate, polyglyceryl-4 diisostearate/polyhydroxystearate/sebacate, ethylhexyl palmitate, undecane, glycerin, carpobrotus edulis extract, propanediol, argania spinosa kernel oil, silica, tocopheryl acetate, dimethicone, sodium chloride, tridecane, jojoba esters, isostearic acid, copernicia cerifera (carnauba) wax, euphorbia cerifera (candelilla) wax, butyrospermum parkii (shea) butter, hydrogenated castor oil, polyglyceryl-3 polyricinoleate, isopropyl myristate, lecithin, caesalpinia spinosa fruit extract, kappaphycus alvarezii extract, bisabolol, helianthus annuus (sunflower) seed oil, polyhydroxystearic acid, stearalkonium hectorite, isopropyl titanium triisostearate, xanthan gum, tocopherol, citric acid, propylene carbonate, caprylyl glycol, caprylhydroxamic acid, ethylhexylglycerin, sodium benzoate, potassium sorbate, iron oxides (CI 77491, CI 77492, CI 77499).

Questions or comments?

1-800-272-6663

Monday–Friday 6 a.m.–6 p.m. PST

Distributed by Arbonne International, LLC,Greenwood, IN 46143 USA

PRINCIPAL DISPLAY PANEL - 50 mL Tube Carton

arbonne®

100% VEGAN

DERMRESULTS

SOFT FOCUS VEIL
BROAD SPECTRUM
SPF 30 SUNSCREEN

Face Lotion for All Skin Types

1.7 fl. oz. / 50 mL